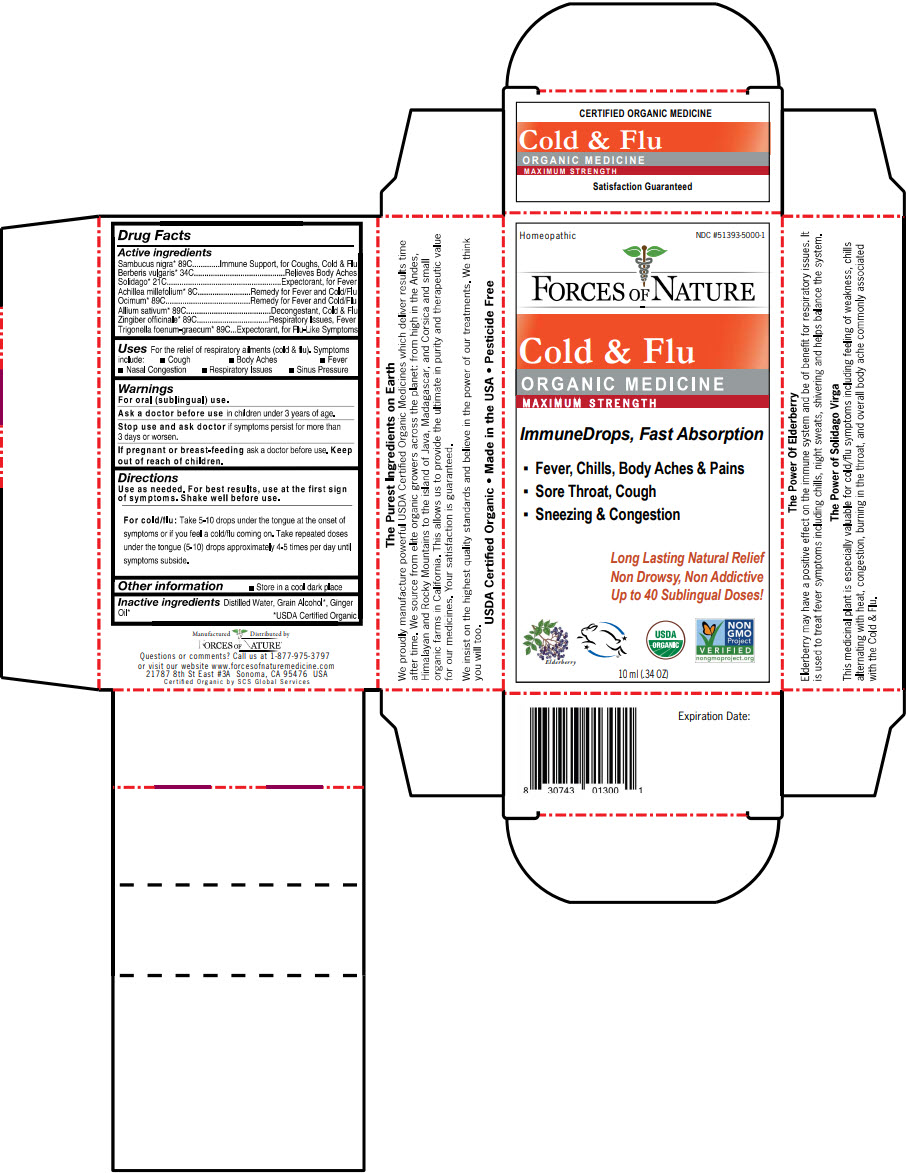 DRUG LABEL: Cold and Flu 
NDC: 51393-5000 | Form: SOLUTION/ DROPS
Manufacturer: Forces of Nature
Category: homeopathic | Type: HUMAN OTC DRUG LABEL
Date: 20210928

ACTIVE INGREDIENTS: EUROPEAN ELDERBERRY 89 [hp_C]/100 mL; BERBERIS VULGARIS ROOT 34 [hp_C]/100 mL; SOLIDAGO CANADENSIS FLOWERING TOP 21 [hp_C]/100 mL; ACHILLEA MILLEFOLIUM FLOWERING TOP 8 [hp_C]/100 mL; HOLY BASIL LEAF 89 [hp_C]/100 mL; GARLIC 89 [hp_C]/100 mL; GINGER 89 [hp_C]/100 mL; FENUGREEK SEED 89 [hp_C]/100 mL
INACTIVE INGREDIENTS: WATER; ALCOHOL; Ginger Oil

Cold & Flu
Maximum Strength

Drug Facts

ACTIVE INGREDIENT

PURPOSE

Active ingredients
Sambucus nigra [USDA Certified Organic] 89C | Immune Support, for Coughs, Cold & Flu
Berberis vulgaris 34C | Relieves Body Aches
Solidago 21C | Expectorant, for Fever
Achillea millefolium 8C | Remedy for Fever and Cold/Flu
Ocimum 89C | Remedy for Fever and Cold/Flu
Allium sativum 89C | Decongestant, Cold & Flu
Zingiber officinale 89C | Respiratory Issues, Fever
Trigonella foenum-graecum 89C | Expectorant, for Flu-Like Symptoms

Uses

For the relief of respiratory ailments (cold & flu). Symptoms include:

- Cough
- Body Aches
- Fever
- Nasal Congestion
- Respiratory Issues
- Sinus Pressure

Warnings

For oral (sublingual) use.

Ask a doctor before use in children under 3 years of age.

Stop use and ask doctor if symptoms persist for more than 3 days or worsen.

PREGNANCY OR BREAST FEEDING

If pregnant or breast-feeding ask a doctor before use.

Keep out of reach of children.

Directions

Use as needed. For best results, use at the first sign of symptoms. Shake well before use.

For cold/flu

Take 5-10 drops under the tongue at the onset of symptoms or if you feel a cold/flu coming on. Take repeated doses under the tongue (5-10) drops approximately 4-5 times per day until symptoms subside.

Other information

- Store in a cool dark place

Inactive ingredients

Distilled Water, Grain Alcohol, Ginger Oil

Questions or comments?

Call us at 1-877-975-3797 or visit our website www.forcesofnaturemedicine.com

Manufactured Distributed by
FORCES OF NATURE®
21787 8th St East #3A Sonoma, CA 95476 USA

PRINCIPAL DISPLAY PANEL - 10 ml Bottle Carton

Homeopathic
NDC #51393-5000-1

FORCES OF NATURE

Cold & Flu
ORGANIC MEDICINE
MAXIMUM STRENGTH

ImmuneDrops, Fast Absorption

- Fever, Chills, Body Aches & Pains
- Sore Throat, Cough
- Sneezing & Congestion

Long Lasting Natural Relief
Non Drowsy, Non Addictive
Up to 40 Sublingual Doses!

Elderberry

USDA
ORGANIC

NON
GMO
Project
VERIFIED
nongmoproject.org

10 ml (.34 OZ)